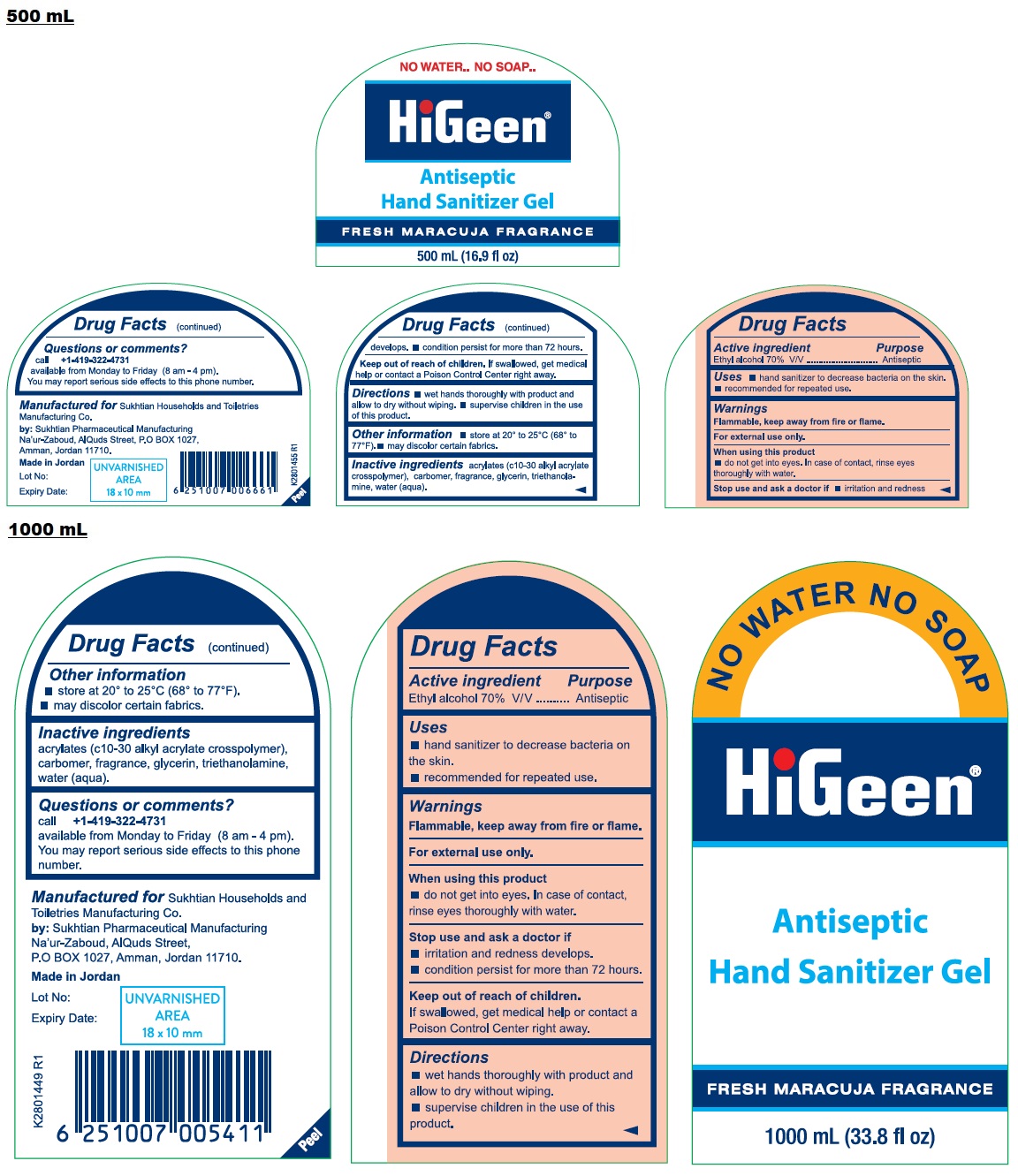 DRUG LABEL: HiGeen Antiseptic Hand Sanitizer Gel FRESH MARACUJA FRAGRANCE
NDC: 71490-040 | Form: GEL
Manufacturer: SUKHTIAN-HTM ( HOUSEHOLDS & TOILETRIES MFG.CO)
Category: otc | Type: HUMAN OTC DRUG LABEL
Date: 20230303

ACTIVE INGREDIENTS: ALCOHOL 70 mL/100 mL
INACTIVE INGREDIENTS: CARBOMER INTERPOLYMER TYPE A (ALLYL SUCROSE CROSSLINKED); CARBOMER HOMOPOLYMER, UNSPECIFIED TYPE; GLYCERIN; TROLAMINE; WATER

HiGeen Antiseptic Hand Sanitizer Gel FRESH MARACUJA FRAGRANCE

Active ingredient

Ethyl alcohol 70% V/V

Purpose

Antiseptic

Uses

• hand sanitizer to decrease bacteria on the skin.
• recommended for repeated use.

Warnings

Flammable, keep away from fire or flame.

For external use only.

When using this product
• do not get into eyes. In case of contact, rinse eyes thoroughly with water.

Stop use and ask a doctor if
• irritation and redness develops.
• condition persist for more than 72 hours.

Keep out of reach of children.
If swallowed, get medical help or contact a Poison Control Center right away.

Directions

• wet hands thoroughly with product and allow to dry without wiping.
• supervise children in the use of this product.

Other information

• store at 20° to 25°C (68° to 77°F).
• may discolor certain fabrics.

Inactive ingredients

acrylates (c10-30 alkyl acrylate crosspolymer), carbomer, fragrance, glycerin, triethanolamine, water (aqua).

Questions or comments?

call +1-419-322-4731
available from Monday to Friday (8 am – 4 pm).
You may report serious side effects to this phone number.

NO WATER
NO SOAP

Manufactured for
Sukhtian Households and Toiletries Manufacturing Co.
by: Sukhtian Pharmaceutical Manufacturing
Na'ur-Zaboud, AlQuds Street,
P.O.BOX 1027, Amman, Jordan 11710.
Made in Jordan